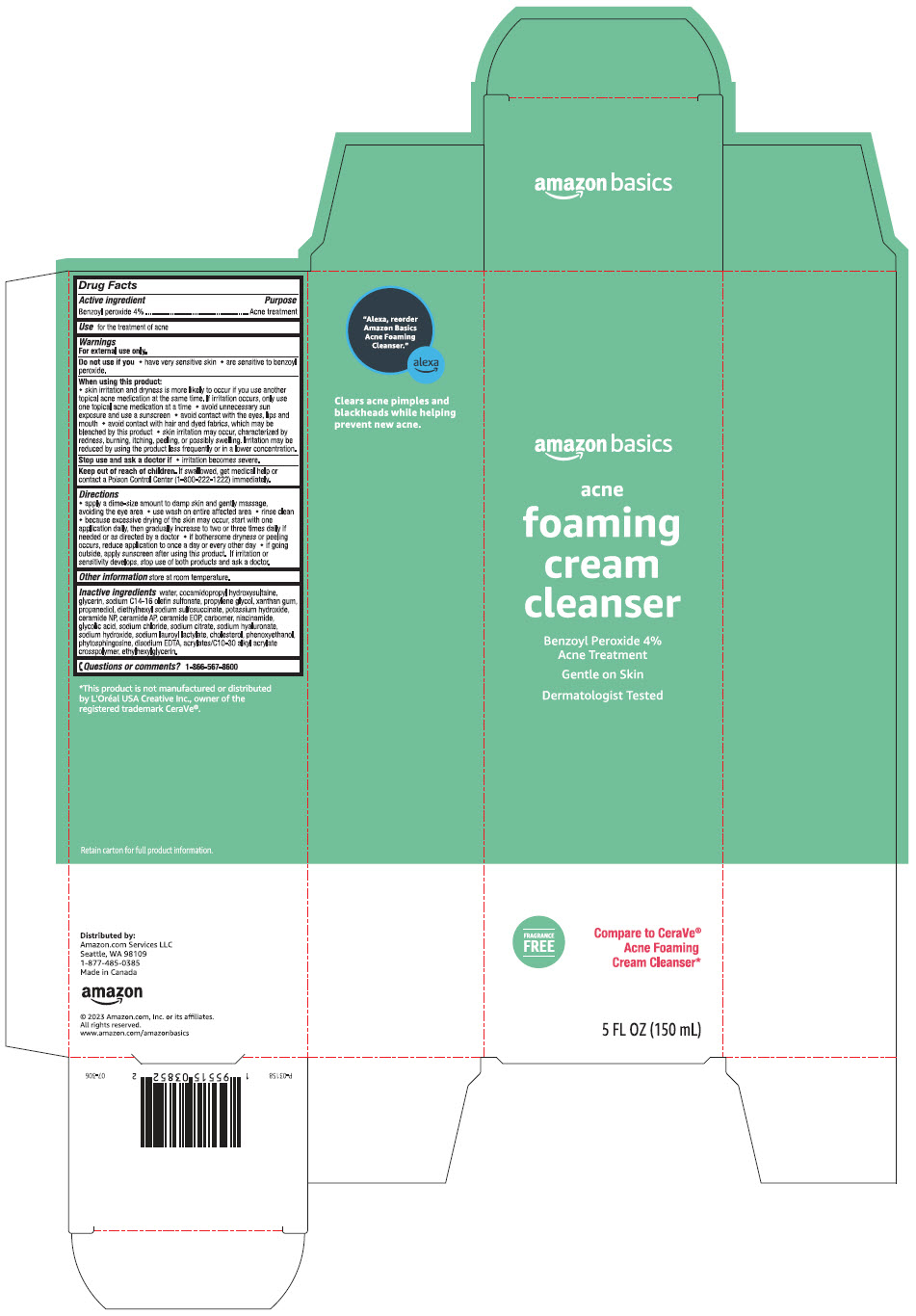 DRUG LABEL: amazon basics acne foaming cleanser
NDC: 72288-852 | Form: LOTION
Manufacturer: AMAZON.COM SERVICES LLC
Category: otc | Type: HUMAN OTC DRUG LABEL
Date: 20241114

ACTIVE INGREDIENTS: BENZOYL PEROXIDE 40 mg/1 mL
INACTIVE INGREDIENTS: Water; Cocamidopropyl Hydroxysultaine; Glycerin; Sodium C14-16 Olefin Sulfonate; Propylene Glycol; Xanthan Gum; Propanediol; DOCUSATE SODIUM; Potassium Hydroxide; Ceramide NP; Ceramide AP; CERAMIDE 1; CARBOMER HOMOPOLYMER, UNSPECIFIED TYPE; Niacinamide; Glycolic Acid; Sodium Chloride; SODIUM CITRATE, UNSPECIFIED FORM; HYALURONATE SODIUM; Sodium Hydroxide; Sodium Lauroyl Lactylate; Cholesterol; Phenoxyethanol; Phytosphingosine; EDETATE DISODIUM; Ethylhexylglycerin

amazon basics acne foaming cream cleanser
Acne Treatment

Drug Facts

Active ingredient

Benzoyl peroxide 4%

Purpose

Acne Medication

Use

for the treatment of acne

Warnings

For external use only

Do not use if you

- have very sensitive skin
- are sensitive to benzoyl peroxide.

When using this product

- skin irritation and dryness is more likely to occur if you use another topical acne medication at the same time. If irritation occurs, only use one topical acne medication at a time.
- avoid unnecessary sun exposure and use a sunscreen
- avoid contact with the eyes, lips, and mouth
- avoid contact with hair and dyed fabrics, which may be bleached by this product
- skin irritation may occur, characterized by redness, burning, itching, peeling, or possibly swelling. Irritation may be reduced by using the product less frequently or in a lower concentration.

Stop use and consult a doctor if

- irritation becomes severe.

Keep out of reach of children. If swallowed, get medical help or contact a Poison Control Center (1-800-222-1222) immediately.

Directions

- apply a dime-size amount to damp skin and gently massage, avoiding the eye area
- use wash on entire affected area
- rinse clean
- because excessive drying of the skin may occur, start with one application daily, then gradually increase to two to three times daily if needed or as directed by a doctor
- if bothersome dryness or peeling occurs, reduce application to once a day or every other day
- if going outside, apply sunscreen after using this product. If irritation or sensitivity develops, stop use of both products and ask a doctor.

Other information

store at room temperature.

Inactive ingredients

water, cocamidopropyl hydroxysultaine, glycerin, sodium C14-16 olefin sulfonate, propylene glycol, xanthan gum, propanediol, diethylhexyl sodium sulfosuccinate, potassium hydroxide, ceramide NP, ceramide AP. ceramide EOP, carbomer, niacinamide, glycolic acid, sodium chloride, sodium citrate, sodium hyaluronate, sodium hydroxide, sodium lauroyl lactylate, cholesterol, phenoxyethanol, phytosphingosine, disodium EDTA, acrylates/C10-30 alkyl acrylate crosspolymer, ethylhexyllycerin.

Questions or comments?

1-866-567-8600

Distributed by:
Amazon.com Services LLC
Seattle, WA 98109

PRINCIPAL DISPLAY PANEL - 150 mL Tube Carton

amazon basics

acne

foaming
cream
cleanser

Benzoyl Peroxide 4%
Acne Treatment

Gentle on Skin

Dermatologist Tested

FRAGRANCE
FREE

Compare to CeraVe®
Acne Foaming
Cream Cleanser*

5 FL OZ (150 mL)